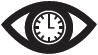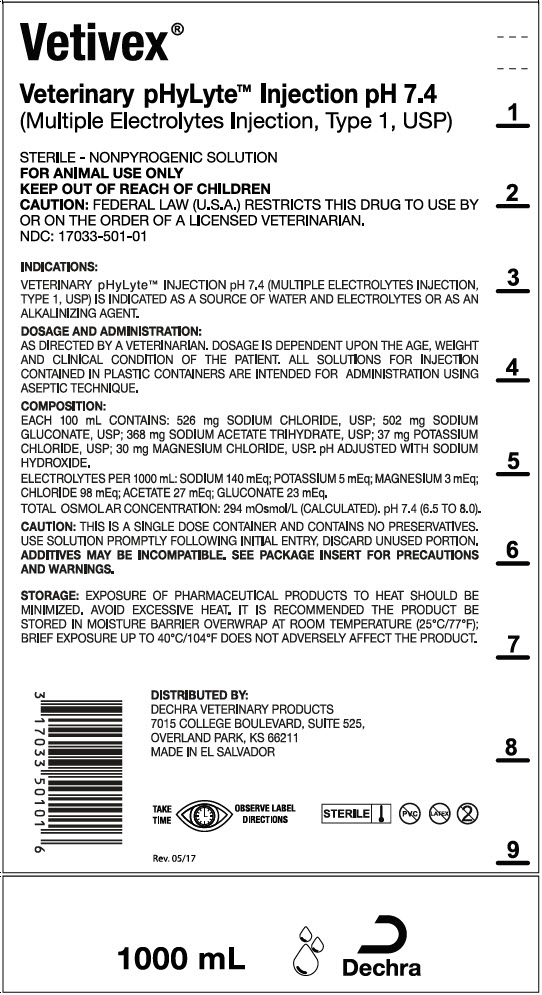 DRUG LABEL: Vetivex Veterinary pHyLyte
NDC: 17033-501 | Form: INJECTION, SOLUTION
Manufacturer: Dechra Veterinary Products
Category: animal | Type: PRESCRIPTION ANIMAL DRUG LABEL
Date: 20200908

ACTIVE INGREDIENTS: Sodium chloride 526 mg/100 mL; Sodium Gluconate 502 mg/100 mL; Sodium Acetate 368 mg/100 mL; Potassium Chloride 37 mg/100 mL; Magnesium Chloride 30 mg/100 mL
INACTIVE INGREDIENTS: Water

Vetivex®
Veterinary pHyLyte® Injection pH 7.4
(Multiple Electrolytes Injection, Type 1, USP)

For Animal Use Only

Description:

Veterinary pHyLyte® Injection pH 7.4 (Multiple Electrolytes Injection, Type 1, USP) is a sterile, nonpyrogenic isotonic solution for fluid and electrolyte replenishment in single dose containers for intravenous administration. It contains no antimicrobial agents or preservatives. Discard unused portion. The pH is adjusted with sodium hydroxide.

Table 1: Veterinary pHyLyte® Injection pH 7.4 (Multiple Electrolytes Injection, Type 1, USP)
Size (mL) | Composition (mg/100mL) |  |  |  |  |  |  | Ionic Concentration (mEq/L) |  |  |  |  |  | kcal/L
Size (mL) | Sodium Chloride, USP (NaCl) | Sodium Gluconate, USP (C6H11NaO7) | Sodium Acetate Trihydrate, USP (C2H3NaO2∙3H2O) | Potassium Chloride, USP (KCl) | Magnesium Chloride, USP (MgCl2∙6H2O) | Osmolarity (mOsmol/L) (calc) | pH | Sodium | Potassium | Magnesium | Chloride | Acetate | Gluconate | Caloric Content
1000 | 526 | 502 | 368 | 37 | 30 | 294 | 7.4 (6.5 to 8.0) | 140 | 5 | 3 | 98 | 27 | 23 | 21
3000 | 526 | 502 | 368 | 37 | 30 | 294 | 7.4 (6.5 to 8.0) | 140 | 5 | 3 | 98 | 27 | 23 | 21
5000 | 526 | 502 | 368 | 37 | 30 | 294 | 7.4 (6.5 to 8.0) | 140 | 5 | 3 | 98 | 27 | 23 | 21

Clinical Pharmacology:

Veterinary pHyLyte® Injection pH 7.4 (Multiple Electrolytes Injection, Type 1, USP) administered intravenously has value as a source of water and electrolytes. It is capable of inducing diuresis, depending on the clinical condition of the patient.

Veterinary pHyLyte® Injection pH 7.4 (Multiple Electrolytes Injection, Type 1, USP) produces a metabolic alkalinizing effect. Acetate and gluconate ions are metabolized ultimately to carbon dioxide and water, which requires the consumption of hydrogen cations.

Indications and Usage:

Veterinary pHyLyte® Injection pH 7.4 (Multiple Electrolytes Injection, Type 1, USP) is indicated as a source of water and electrolytes or as an alkalinizing agent.

Veterinary pHyLyte® Injection pH 7.4 (Multiple Electrolytes Injection, Type 1, USP) is compatible with blood or blood components. It may be administered prior to or following the infusion of blood through the same administration set (i.e. as a priming solution), added to or infused concurrently with blood components, or used as a diluent in the transfusion of packed erythrocytes. Veterinary pHyLyte® Injection pH 7.4 (Multiple Electrolytes Injection, Type 1, USP) and 0.9% Sodium Chloride Injection, USP are equally compatible with blood or blood components.

Contraindications:

None known.

Warnings:

Veterinary pHyLyte® Injection pH 7.4 (Multiple Electrolytes Injection, Type 1, USP) should be used with great care, if at all, in patients with congestive heart failure, severe renal insufficiency, and in clinical states in which there exists edema with sodium retention.

Veterinary pHyLyte® Injection pH 7.4 (Multiple Electrolytes Injection, Type 1, USP) should be used with great care, if at all, in patients with hyperkalemia, severe renal failure, and in conditions in which potassium retention is present.

Veterinary pHyLyte® Injection pH 7.4 (Multiple Electrolytes Injection, Type 1, USP) should be used with great care in patients with metabolic or respiratory alkalosis. The administration of acetate or gluconate ions should be done with great care in those conditions in which there is an increased level or an impaired utilization of these ions, such as severe hepatic insufficiency.

The intravenous administration of Veterinary pHyLyte® Injection pH 7.4 (Multiple Electrolytes Injection, Type 1, USP) can cause fluid and/or solute overloading resulting in dilution of serum electrolyte concentrations, overhydration, congested states, or pulmonary edema. The risk of dilutional states is inversely proportional to the electrolyte concentrations of the injection. The risk of solute overload causing congested states with peripheral and pulmonary edema is directly proportional to the electrolyte concentrations of the injection.

In patients with diminished renal function, administration of Veterinary pHyLyte® Injection pH 7.4 (Multiple Electrolytes Injection, Type 1, USP) may result in sodium or potassium retention.

Adverse Reactions:

Reactions which may occur because of the solution or the technique of administration include febrile response, infection at the site of injection, venous thrombosis or phlebitis extending from the site of injection, extravasation, and hypervolemia. If an adverse reaction does occur, discontinue the infusion, evaluate the patient, institute appropriate therapeutic countermeasures and save the remainder of the fluid for examination if deemed necessary.

Precautions:

Clinical evaluation and periodic laboratory determinations are necessary to monitor changes in fluid balance, electrolyte concentrations, and acid base balance during prolonged parenteral therapy or whenever the condition of the patient warrants such evaluation.

Veterinary pHyLyte® Injection pH 7.4 (Multiple Electrolytes Injection, Type 1, USP) should be used with caution. Excess administration may result in metabolic alkalosis.

Caution must be exercised in the administration of Veterinary pHyLyte® Injection pH 7.4 (Multiple Electrolytes Injection, Type 1, USP) to patients receiving corticosteroids or corticotropin.

Do not administer unless solution is clear and seal is intact.

Dosage and Administration

As directed by a veterinarian. Dosage is dependent upon the age, weight and clinical condition of the patient as well as laboratory determinations.

Parenteral drug products should be inspected visually for particulate matter and discoloration prior to administration whenever solution and container permit.

All injections in plastic containers are intended for intravenous administration using sterile equipment.

Additives may be incompatible. Complete information is not available. Those additives known to be incompatible should not be used. Consult with pharmacist, if available. If, in the informed judgment of the veterinarian, it is deemed advisable to introduce additives, use aseptic technique. Mix thoroughly when additives have been introduced. Do not store solutions containing additives. Discard unused portion.

Overdosage

In an event of overhydration or solute overload, re-evaluate the patient and institute appropriate corrective measures. See Warnings, Precautions and Adverse Events.

How Supplied:

Veterinary pHyLyte® Injection pH 7.4 (Multiple Electrolytes Injection, Type 1, USP) in plastic container is available as follows:

NDC Code | Volume
17033-501-01 | 1000 mL [PVC Free, DEHP Free and Latex Free Bag.]
17033-501-03 | 3000 mL [The plastic container is fabricated from a specially formulated polyvinyl chloride. The amount of water that can permeate from inside the container into the overwrap is insufficient to affect the solution significantly. Solutions in contact with the plastic container can leach out certain of its chemical components in very small amounts within the expiration period, e.g., di-2-ethylhexyl phthalate (DEHP), up to 5 parts per million. However, the safety of the plastic has been confirmed in animals according to USP biological tests for plastic containers, as well as tissue culture toxicity studies.]
17033-501-05 | 5000 mL

Storage:

Exposure of pharmaceutical products to heat should be minimized. Avoid excessive heat. It is recommended the product be stored in the moisture barrier overwrap at room temperature (25ºC/77ºF); brief exposure up to 40ºC/104ºF does not adversely affect the product.

Directions for use of plastic container

To Open

Tear overwrap down side at slit and remove solution container. Some opacity of the plastic due to moisture absorption during the sterilization process may be observed. This is normal and does not affect the solution quality or safety. The opacity will diminish gradually. Check for minute leaks by squeezing inner bag firmly. If leaks are found, discard solution as sterility may be impaired.

If supplemental medication is desired, follow directions below.

Preparation for Administration

1. Suspend container from eyelet support.
2. Remove protector from outlet port at bottom of container.
3. Attach administration set. Refer to complete directions accompanying set.

To Add Medication

WARNING: Additives may be incompatible.

To add medication before solution administration

1. Prepare medication site.
2. Using syringe with 19 to 22 gauge needle, puncture resealable medication port and inject.
3. Mix solution and medication thoroughly. For high density medication such as potassium chloride, squeeze ports while ports are upright and mix thoroughly.

To add medication during solution administration

1. Close clamp on the administration set to stop the flow to the patient.
2. Prepare medication site.
3. Using syringe with 19 to 22 gauge needle, puncture resealable medication port and inject.
4. Remove container from IV pole and/or turn to an upright position.
5. Evacuate both ports by squeezing them while container is in the upright position.
6. Mix solution and medication thoroughly.
7. Return container to in-use position and continue administration.

CAUTION: Federal law (USA) restricts this drug to use by or on the order of a licensed veterinarian.

Distributed by:
Dechra Veterinary Products
7015 College Boulevard, Suite 525,
Overland Park, KS 66211

TAKE TIME |  | OBSERVE LABEL DIRECTIONS

Made in El Salvador
For a copy of the Safety Data Sheet (SDS)
or to report adverse reactions call Dechra Veterinary Products at (866) 933-2472.
VETIVEX® and pHyLyte® are trademarks of Dechra, Ltd; all rights reserved.
© 2017 Dechra Ltd.

REV.10/17

PRINCIPAL DISPLAY PANEL - 1000 mL Container Label

Vetivex®

Veterinary pHyLyte™ Injection pH 7.4
(Multiple Elecrolytes Injection, Type 1, USP)

STERILE - NONPYROGENIC SOLUTION
FOR ANIMAL USE ONLY
KEEP OUT OF REACH OF CHILDREN
CAUTION: FEDERAL LAW (U.S.A.) RESTRICTS THIS DRUG TO USE BY
OR ON THE ORDER OF A LICENSED VETERINARIAN.
NDC: 17033-501-01

1000 mL
Dechra